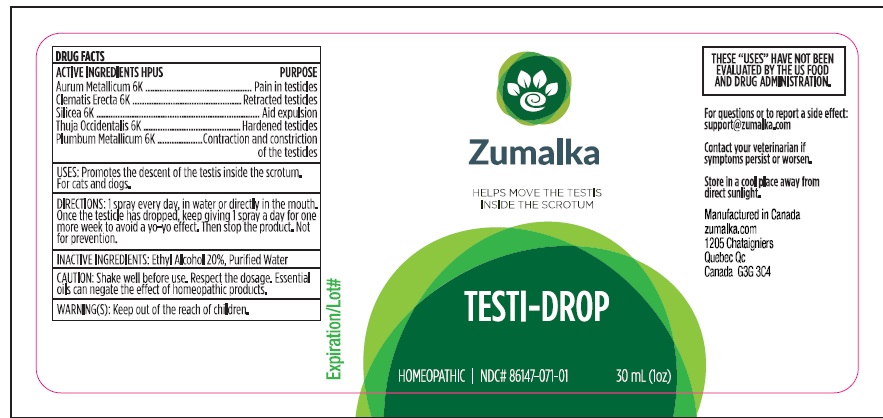 DRUG LABEL: TESTI-DROP
NDC: 86147-071 | Form: LIQUID
Manufacturer: Groupe Cyrenne Inc.
Category: homeopathic | Type: OTC ANIMAL DRUG LABEL
Date: 20251120

ACTIVE INGREDIENTS: GOLD 6 [hp_X]/30 mL; CLEMATIS RECTA FLOWERING TOP 6 [hp_X]/30 mL; SILICON DIOXIDE 6 [hp_X]/30 mL; THUJA OCCIDENTALIS LEAFY TWIG 6 [hp_X]/30 mL; LEAD 6 [hp_X]/30 mL
INACTIVE INGREDIENTS: ALCOHOL; WATER

Active ingredient

Aurum Metallicum 6k, Clematis Erecta 6k, Silicea 6k, Thuja Occidentalis 6k, Plumbum Metallicum 6k

Uses

Promotes the descent of the testis inside the scrotum. For cats and dogs only.

Warnings

Shake well before use. Respect the dosage. Essential oils can negate the effects of homeopathic products. Store at room temperature. Keep out of reach of children.

Direction

1 spray every day, in water or directly in the mouth. Once the testicle has dropped, keep giving 1 spray a day for one more week to avoid a yo-yo effect. Then stop the product. Not for prevention.

Inactive ingredient

Ethyl alcohol 20%, purified water